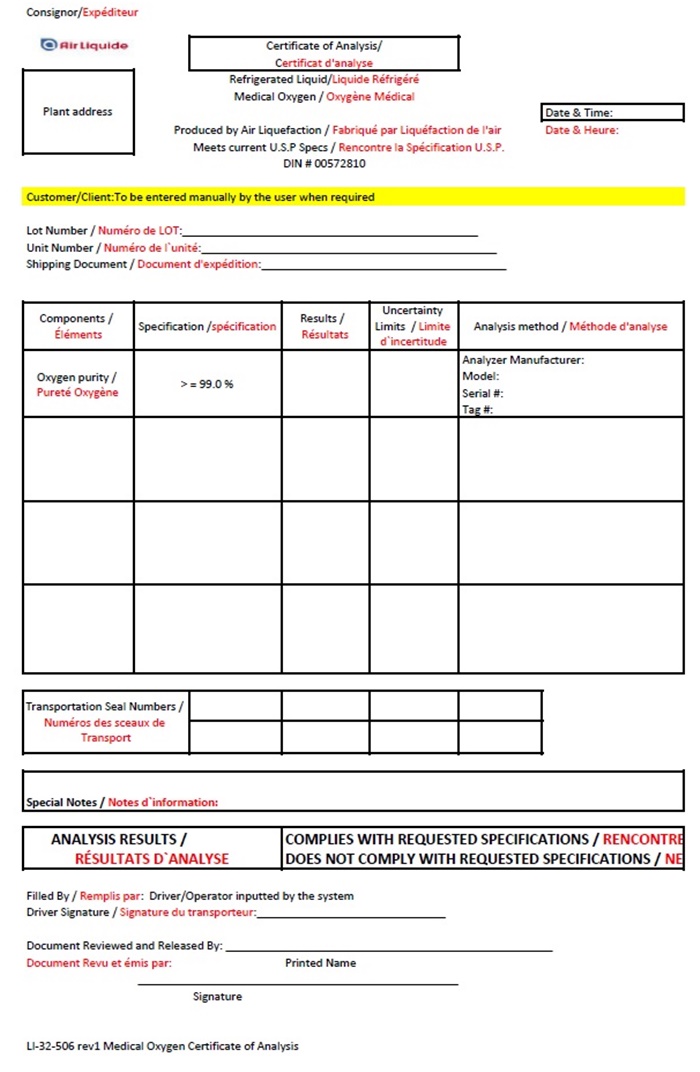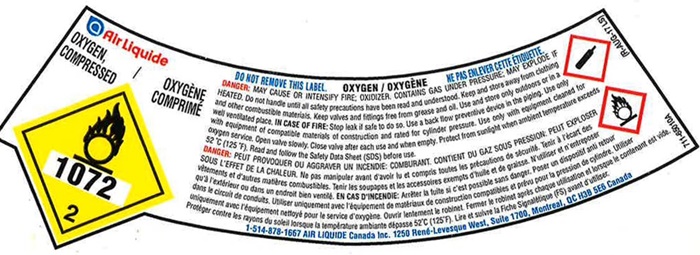 DRUG LABEL: OXYGEN
NDC: 74709-001 | Form: GAS
Manufacturer: Air Liquide Canada Inc
Category: prescription | Type: HUMAN PRESCRIPTION DRUG LABEL
Date: 20241004

ACTIVE INGREDIENTS: OXYGEN 992 mL/1 L

Air Liquide Canada Oxygen 001

Air Liquide Canada Oxygen

Air Liquide

OXYGEN OXYGÈNÈ

COMPRESSED COMPRIMÈ

1072

2

DO NOT REMOVE THIS LABEL OXYGEN / OXYGÈNÈ NE PAS ENLEVER CETTE ÈTIQUETTE

DANGER: MAY CAUSE OR INTENSIFY FIRE; OXIDIZER. CONTAINS GAS UNDER PRESSURE; MAY EXPLODE IF HEATED. Do not handle until all safety precautions have been read and understood. Keep and store away from clothing and other combustible materials. Keep valves and fittings free from grease and oil. Use and store only outdoors or in a well-ventilated place. In case of fire: Stop leak if safe to do so. Use a backflow preventive device in the piping. Use only with equipment of compatible materials of construction and rated for cylinder pressure. Use only with equipment cleaned for oxygen service. Open valve slowly. Close valve after each use and when empty. Protect from sunlight when ambient temperature exceeds 52°C (125° F). Read and follow the Safety Data Sheet (SDS) before use.

DANGER: PEUT PROVOQUER OU AGGRAVER UN INCENDIE: COMBURANT CONTENT DU GAZ SOUS PRESSION: PEUT EXPLOSER SOUS L’EFFET DE LA CHALEUR. No pas manipuler avant d’avoir lu et comprls toutes les precautions de sècuritè. Tenir à rècart des vètements et d’autres mabères combustibles. Tenir les soupapes et les accessoores exempt d’huile et de graisse. N’utiliser et n’entreposer qu’à l’extèrieur ou dans un endroit bien ventilè. EN CAS D’INCENDIE: Arrèter ta tuite si c’est possible sans danger. Poser un dispositive anti retour dans le circuit de conduits. Utilser uniquement avec l’equipement de matèriaux de construction compatibles et prèvu pour la pression de cylinder. Utilser uniquement avec l’èquipement nettoyè pour le service d’oxygène. Ouvrir lentement le robinet. Fermer le robinet apres chaque utilsation et torsque le contentant est vide. Protèger contre les rayons du soleit lorsque la temperature ambiante dèpasse 52°C (125° F). Lire et sulvre la Fiche Signaletique (FS) avant d’utiliser.

1-514-878-1667 AIR LIQUIDE Canada Inc. 1250 Renè-Levesque West, Suite 1700, Montreal, QC H3B 5E6 Canada

Air Liquide Canada Oxygen COA

Consignor/ Expèditeur

Air Liquide Certificate of Analysis

Certificat d’analyse

Plant Address Refrigerated Liquid / Liquide Réfrigéré

Medical Oxygen / Oxygène Médical

Date & Time

Produced by Air Liquefaction / Fabriqué par Liquéfaction de l’air

Meets current U.S.P. Specs / Rencontre la Spécifcation U.S.P.

Customer/Client: To be entered manually by the user when required

Lot Number / Numéro de LOT: __________________

Unit Number / Numéro de l’unité: _______________

Shipping Document / Document d’expédition: ________________

Componets /; Éléments | Specification /; Specification | Results /; Résultats | Uncertainty Limits /; Limite d’incertitude | Analysis method / Méthode d’analyse
Oxygen purity / Pureté Oxygène | >=99.0% |  |  | Analyzer Manufacturer:; Model:; Serial #:; Tag #:

Transportation Seal Numbers / Numéros des sceaux de Transport

Special Notes / Notes d’information:

ANALYSIS RESULTS /

RÉSULTATS D’ANALYSE

COMPLIES WITH REQUESTED SPECIFICATIONS / RENCONTRE

DOES NOT COMPLY WITH REQUESTED SPECIFICATIONS / NE

Filled By / Remplis par: Driver / Operator inputted by the system

Driver Signature / Signature du transporteur: ______________________________

Document Reviewed and Released By: ___________________________________

Printed Name

Document Revu et émis par:

______________________________________________________

Signature

LI-32-506 rev 1 Medical Oxygen Certificate of Analysis